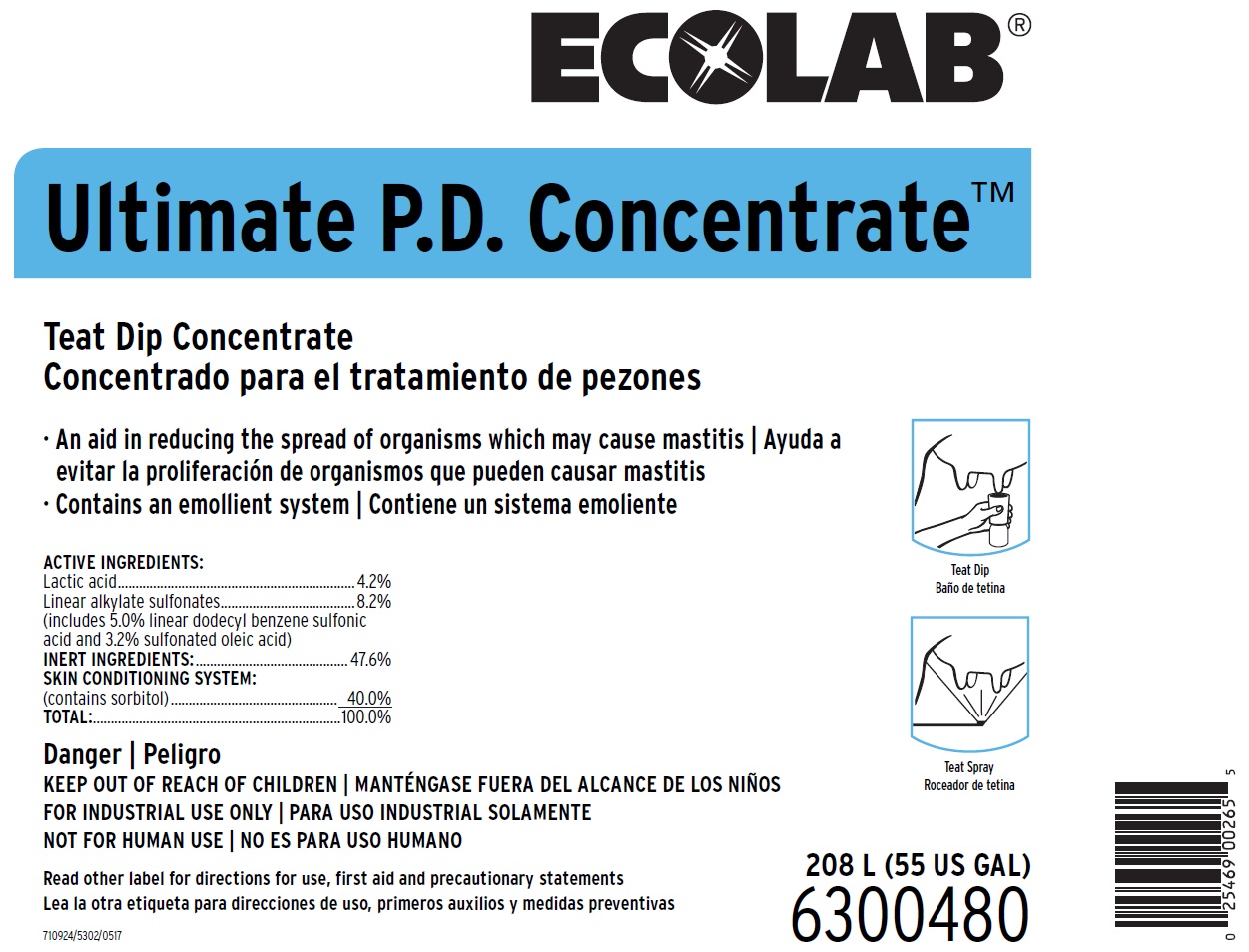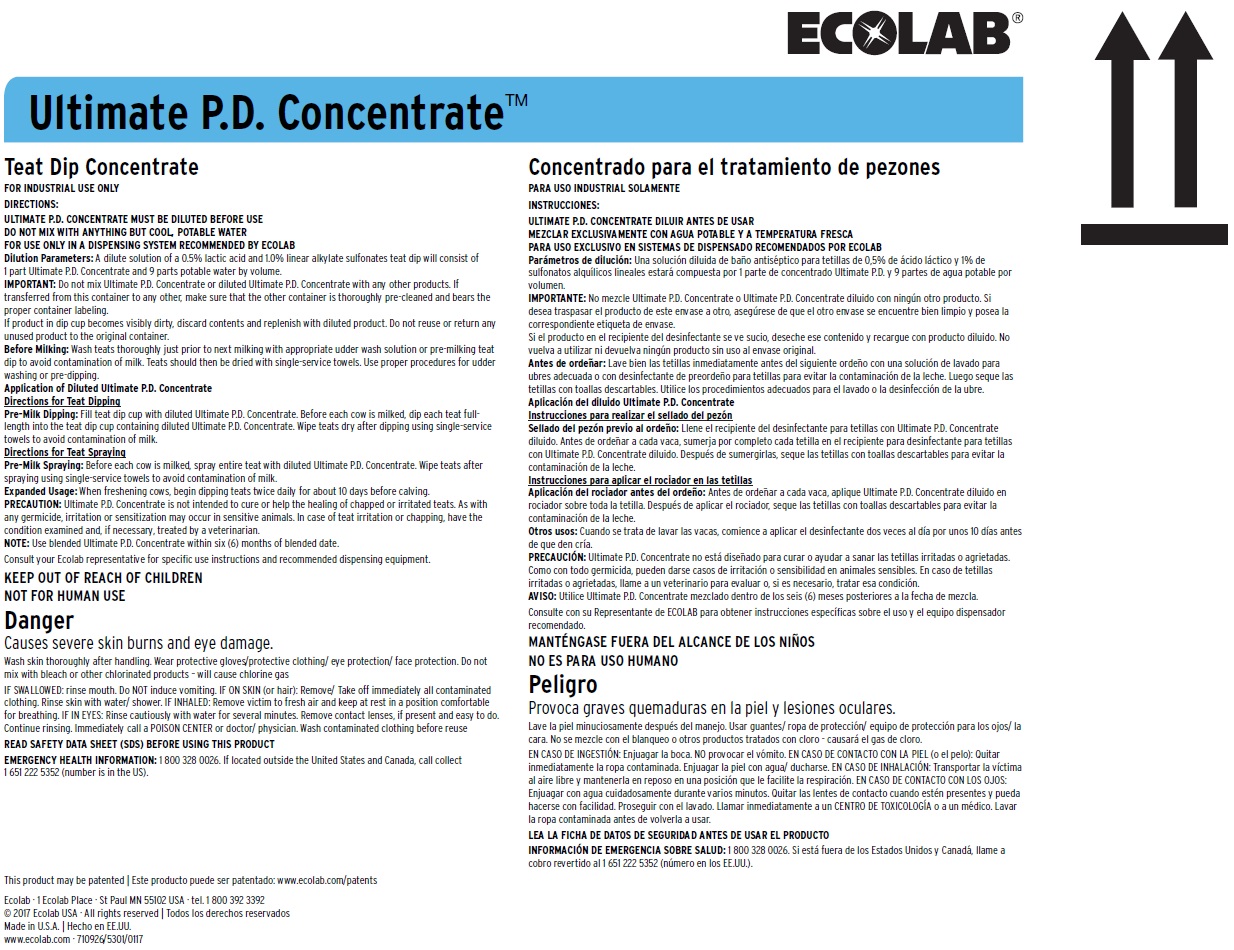 DRUG LABEL: Ultimate P.D. Concentrate
NDC: 47593-494 | Form: SOLUTION
Manufacturer: Ecolab Inc.
Category: animal | Type: OTC ANIMAL DRUG LABEL
Date: 20250902

ACTIVE INGREDIENTS: LACTIC ACID 42 mg/1 mL; DODECYLBENZENESULFONIC ACID 50 mg/1 mL; POTASSIUM SULFOOLEATE 32 mg/1 mL
INACTIVE INGREDIENTS: SORBITOL; WATER

SAFE HANDLING WARNING

Danger

Causes severe skin burns and eye damage.

Wash skin thoroughly after handling. Wear protective gloves/protective clothing/ eye protection/ face protection. Do not mix with bleach or other chlorinated products – will cause chlorine gas

IF SWALLOWED: rinse mouth. Do NOT induce vomiting. IF ON SKIN (or hair): Remove/ Take off immediately all contaminated clothing. Rinse skin with water/ shower. IF INHALED: Remove victim to fresh air and keep at rest in a position comfortable for breathing. IF IN EYES: Rinse cautiously with water for several minutes. Remove contact lenses, if present and easy to do. Continue rinsing. Immediately call a POISON CENTER or doctor/ physician. Wash contaminated clothing before reuse

DIRECTIONS:
ULTIMATE P.D. CONCENTRATE MUST BE DILUTED BEFORE USE
DO NOT MIX WITH ANYTHING BUT COOL, POTABLE WATER
FOR USE ONLY IN A DISPENSING SYSTEM RECOMMENDED BY ECOLAB
Dilution Parameters: A dilute solution of a 0.5% lactic acid and 1.0% linear alkylate sulfonates teat dip will consist of
1 part Ultimate P.D. Concentrate and 9 parts potable water by volume.
IMPORTANT: Do not mix Ultimate P.D. Concentrate or diluted Ultimate P.D. Concentrate with any other products. If transferred from this container to any other, make sure that the other container is thoroughly pre-cleaned and bears the proper container labeling.
If product in dip cup becomes visibly dirty, discard contents and replenish with diluted product. Do not reuse or return any unused product to the original container.
Before Milking: Wash teats thoroughly just prior to next milking with appropriate udder wash solution or pre-milking teat dip to avoid contamination of milk. Teats should then be dried with single-service towels. Use proper procedures for udder washing or pre-dipping.
Application of Diluted Ultimate P.D. Concentrate
Directions for Teat Dipping
Pre-Milk Dipping: Fill teat dip cup with diluted Ultimate P.D. Concentrate. Before each cow is milked, dip each teat full-length into the teat dip cup containing diluted Ultimate P.D. Concentrate. Wipe teats dry after dipping using single-service towels to avoid contamination of milk.
Directions for Teat Spraying
Pre-Milk Spraying: Before each cow is milked, spray entire teat with diluted Ultimate P.D. Concentrate. Wipe teats after spraying using single-service towels to avoid contamination of milk.
Expanded Usage: When freshening cows, begin dipping teats twice daily for about 10 days before calving.
PRECAUTION: Ultimate P.D. Concentrate is not intended to cure or help the healing of chapped or irritated teats. As with any germicide, irritation or sensitization may occur in sensitive animals. In case of teat irritation or chapping, have the condition examined and, if necessary, treated by a veterinarian.
NOTE: Use blended Ultimate P.D. Concentrate within six (6) months of blended date.
Consult your Ecolab representative for specific use instructions and recommended dispensing equipment.

OTHER SAFETY INFORMATION

Danger

KEEP OUT OF REACH OF CHILDREN

FOR INDUSTRIAL USE ONLY

NOT FOR HUMAN USE

Read other label for directions for use, first aid and precautionary statements

READ SAFETY DATA SHEET (SDS) BEFORE USING THIS PRODUCT

EMERGENCY HEALTH INFORMATION: 1 800 328 0026. If located outside the United States and Canada, call collect 1 651 222 5352 (number is in the US).

Principal Display Panel & Representative Label

ECOLAB

Ultimate P.D. Concentrate

Teat Dip Concentrate

An aid in reducing the spread of organisms which may cause mastitis

Contains an emollient system

ACTIVE INGREDIENTS:

Lactic acid...............................................................4.2%

Linear alkylate sulfonates.......................................8.2%

(includes 5.0% linear dodecyl benzene sulfonic acid and 3.2% sulfonated oleic acid)

INERT INGREDIENTS:............................................47.6%

SKIN CONDITIONING SYSTEM:

(contains sorbitol)................................................ 40.0%

TOTAL:......................................................................100.0%

Danger
KEEP OUT OF REACH OF CHILDREN
FOR INDUSTRIAL USE ONLY
NOT FOR HUMAN USE
Read other label for directions for use, first aid and precautionary statements

208 L (55 US GAL)

710924/5302/0517

6300480